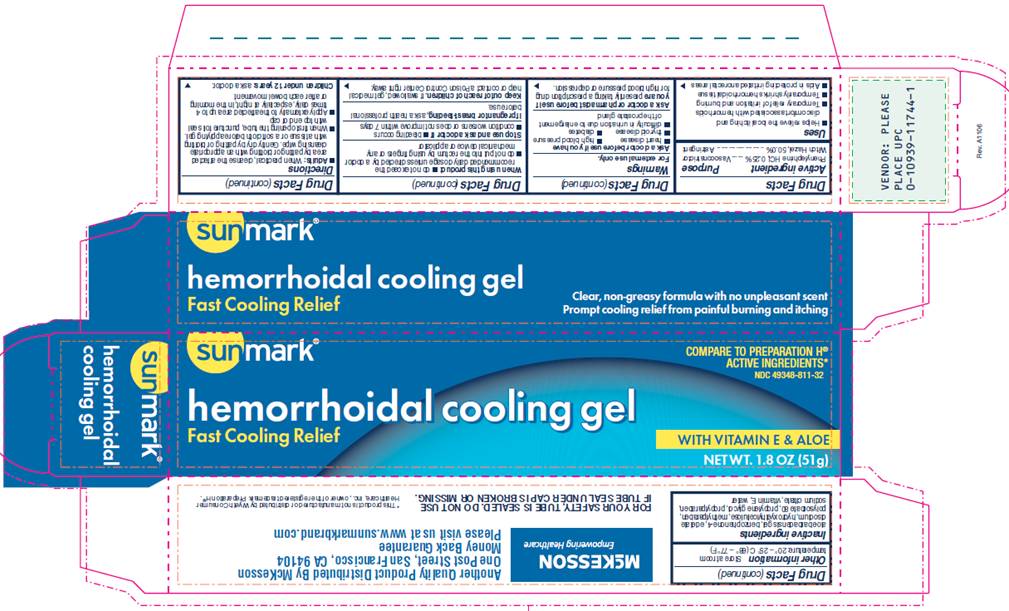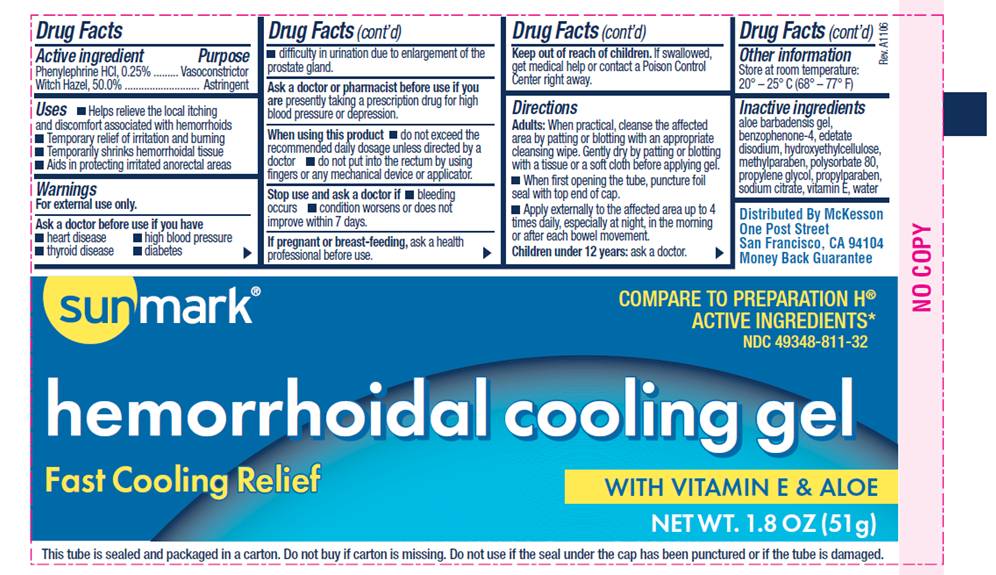 DRUG LABEL: Hemorrhoidal Cooling Gel
NDC: 49348-811 | Form: GEL
Manufacturer: McKesson
Category: otc | Type: HUMAN OTC DRUG LABEL
Date: 20100204

ACTIVE INGREDIENTS: PHENYLEPHRINE HYDROCHLORIDE 0.25 g/1 g; WITCH HAZEL 50 g/1 g
INACTIVE INGREDIENTS: ALOE VERA LEAF; SULISOBENZONE; EDETATE DISODIUM; HYDROXYETHYL CELLULOSE (2000 CPS AT 1%); METHYLPARABEN; POLYSORBATE 80; PROPYLENE GLYCOL; PROPYLPARABEN; SODIUM CITRATE; .ALPHA.-TOCOPHEROL ACETATE, D-; WATER

DRUG FACTS

ACTIVE INGREDIENT

Phenylephrine HCI, 0.25%
Witch Hazel, 50.0%

PURPOSE

Vasoconstrictor
Astringent

USES

- Helps relieve the local itching and discomfort associated with hemorrhoids
- Temporary relief of irritation and burning
- Temporarily shrinks hemorrhoidal tissue
- Aids in protecting irritated anorectal areas

WARNINGS

For external use only.

Ask a doctor before use if you have

- heart disease
- thyroid disease
- high blood pressure
- diabetes
- difficulty in urination due to enlargement of the prostate gland

Ask a doctor or pharmacist before use if you are

presently taking a prescription drug for high blood pressure or depression.

When using this product

- do not exceed the recommended daily dosage unless directed by a doctor
- do not put into the rectum using fingers or any mechanical device or applicator

Stop use and ask a doctor

- if bleeding occurs
- condition worsens or does not improve within 7 days

If pregnant or breastfeeding,

ask a health professional before use.

Keep out of reach of children

If swallowed, get medical help or contact a Poison Control Center right away.

DIRECTIONS

- Adults: when practical, cleanse the affected area by patting or blotting with an appropriate cleansing wipe. Gently dry by patting or blotting with a tissue or a soft cloth before applying gel.
- When first opening the tube, puncture foil seal with top end of cap
- Apply externally to the affected area up to 4 times daily, especially at night, in the morning, or after each bowel movement

Children under 12 years: ask a doctor.

OTHER INFORMATION

Store at room temperature: 20° - 25° C (68° - 77° F)

INACTIVE INGREDIENTS

aloe barbadensis gel, benzophenone-4, edetate disodium, hydroxyethylcellulose, methylparaben, polysorbate 80, propylene glycol, propylparaben, sodium citrate, vitamin E, water

PACKAGE INFORMATION - TUBE

Sunmark®

COMPARE TO PREPARATION H® ACTIVE INGREDIENTS*

NDC 49348-811-32

Hemorrhoidal Cooling Gel

Fast Cooling Relief

WITH VITAMIN E AND ALOE

NET WT. 1.8 OZ (51 g)

This tube is sealed and packaged in a carton. Do not buy if carton is missing. Do not use if the seal under the cap has been punctured or if the tube is damaged.

Distributed by McKesson
One Post Street
San Francisco, CA 94104
Money Back Guarantee

PACKAGE INFORMATION - CARTON

Sunmark®
COMPARE TO PREPARATION H® ACTIVE INGREDIENTS*
NDC 49348-811-32
Hemorrhoidal Cooling Gel
Fast Cooling Relief
Clear, non-greasy formula with no unpleasant scent
Prompt cooling relief from painful burning and itching
WITH VITAMIN E AND ALOE
NET WT. 1.8 OZ (51 g)
Another Quality Product Distributed by McKesson
One Post Street, San Francisco, CA 94104
Money Back Guarantee
Please visit us at www.sunmarkbrand.com
FOR YOUR SAFETY, TUBE IS SEALED. DO NOT USE IF TUBE SEAL UNDER CAP IS BROKEN OR MISSING.
*This product is not manufactured by Wyeth Consumer Healthcare, Inc., owner of the registered trademark Preparation H®.